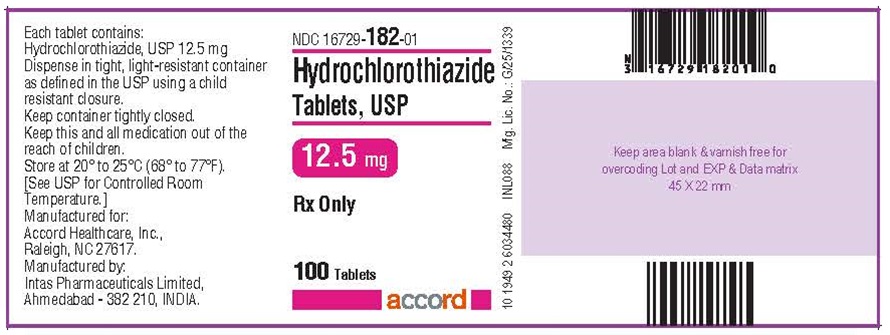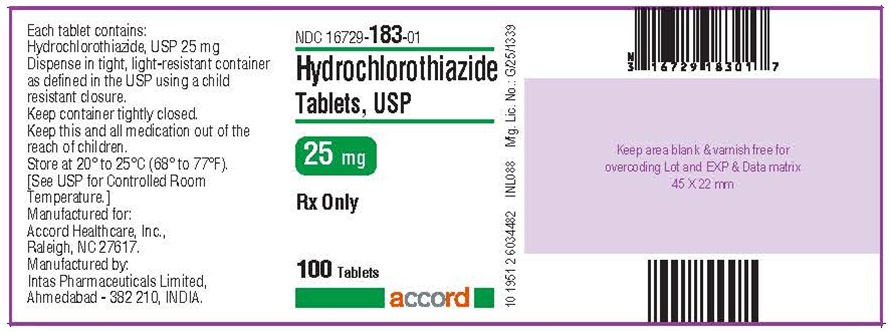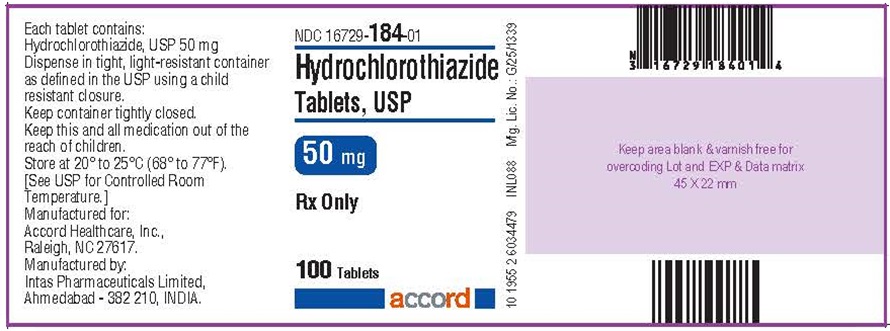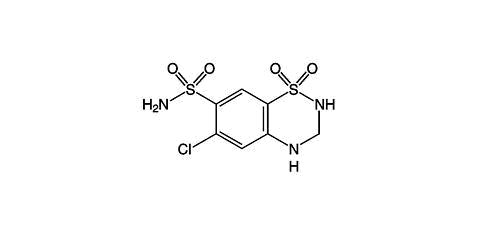 DRUG LABEL: Hydrochlorothiazide
NDC: 16729-182 | Form: TABLET
Manufacturer: Accord Healthcare Inc.
Category: prescription | Type: HUMAN PRESCRIPTION DRUG LABEL
Date: 20260224

ACTIVE INGREDIENTS: HYDROCHLOROTHIAZIDE 12.5 mg/1 1
INACTIVE INGREDIENTS: CALCIUM PHOSPHATE, DIBASIC, DIHYDRATE; FD&C YELLOW NO. 6; LACTOSE MONOHYDRATE; MAGNESIUM STEARATE; STARCH, CORN; SODIUM STARCH GLYCOLATE TYPE A POTATO

HYDROCHLOROTHIAZIDE TABLETS, USP
12.5 mg, 25 mg and 50 mg
Rx only

DESCRIPTION:

Hydrochlorothiazide is a diuretic and antihypertensive. It is the 3,4-dihydro derivative of chlorothiazide. It is chemically designated as 6-chloro-3,4-dihydro-2 H-1,2,4-benzothiadiazine-7-sulfonamide 1,1-dioxide and has the following structural formula:

C7H8CIN3O4S2 M.W. 297.74

Hydrochlorothiazide, USP is a white, or practically white, crystalline powder which is slightly soluble in water, freely soluble in sodium hydroxide solution, in n-butylamine, and in dimethylformamide; sparingly soluble in methanol; insoluble in ether, in chloroform, and in dilute mineral acids. Each tablet for oral administration contains 12.5 mg, 25 mg or 50 mg hydrochlorothiazide, USP. In addition, each tablet contains the following inactive ingredients: dibasic calcium phosphate dihydrate, FD & C yellow, lactose monohydrate, magnesium stearate, pregelatinized starch (starch 1500) and sodium starch glycolate.

CLINICAL PHARMACOLOGY:

The mechanism of the antihypertensive effect of thiazides is unknown. Hydrochlorothiazide does not usually affect normal blood pressure.

Hydrochlorothiazide affects the distal renal tubular mechanism of electrolyte reabsorption. At maximal therapeutic dosage all thiazides are approximately equal in their diuretic efficacy.

Hydrochlorothiazide increases excretion of sodium and chloride in approximately equivalent amounts. Natriuresis may be accompanied by some loss of potassium and bicarbonate.

After oral use diuresis begins within 2 hours, peaks in about 4 hours and lasts about 6 to 12 hours.

PHARMACOKINETICS

Pharmacokinetics and Metabolism:Hydrochlorothiazide is not metabolized but is eliminated rapidly by the kidney. When plasma levels have been followed for at least 24 hours, the plasma half-life has been observed to vary between 5.6 and 14.8 hours. At least 61% of the oral dose is eliminated unchanged within 24 hours. Hydrochlorothiazide crosses the placental but not the blood-brain barrier and is excreted in breast milk.

INDICATIONS AND USAGE:

Hydrochlorothiazide tablets are indicated as adjunctive therapy in edema associated with congestive heart failure, hepatic cirrhosis, and corticosteroid and estrogen therapy.

Hydrochlorothiazide tablets have also been found useful in edema due to various forms of renal dysfunction such as nephrotic syndrome, acute glomerulonephritis, and chronic renal failure.

Hydrochlorothiazide tablets are indicated in the management of hypertension either as the sole therapeutic agent or to enhance the effectiveness of other antihypertensive drugs in the more severe forms of hypertension.

USE IN SPECIFIC POPULATIONS

Use in Pregnancy:Routine use of diuretics during normal pregnancy is inappropriate and exposes mother and fetus to unnecessary hazard. Diuretics do not prevent development of toxemia of pregnancy and there is no satisfactory evidence that they are useful in the treatment of toxemia.

Edema during pregnancy may arise from pathologic causes or from the physiologic and mechanical consequences of pregnancy. Thiazides are indicated in pregnancy when edema is due to pathologic causes, just as they are in the absence of pregnancy (see PRECAUTIONS: Pregnancy). Dependent edema in pregnancy, resulting from restriction of venous return by the gravid uterus, is properly treated through elevation of the lower extremities and use of support stockings. Use of diuretics to lower intravascular volume in this instance is illogical and unnecessary. During normal pregnancy there is hypervolemia which is not harmful to the fetus or the mother in the absence of cardiovascular disease. However, it may be associated with edema, rarely generalized edema. If such edema causes discomfort, increased recumbency will often provide relief. Rarely this edema may cause extreme discomfort which is not relieved by rest. In these instances, a short course of diuretic therapy may provide relief and be appropriate.

CONTRAINDICATIONS:

Anuria.

Hypersensitivity to this product or to other sulfonamide-derived drugs.

WARNINGS:

Use with caution in severe renal disease. In patients with renal disease, thiazides may precipitate azotemia. Cumulative effects of the drug may develop in patients with impaired renal function.

Thiazides should be used with caution in patients with impaired hepatic function or progressive liver disease, since minor alterations of fluid and electrolyte balance may precipitate hepatic coma.

Thiazides may add to or potentiate the action of other antihypertensive drugs.

Sensitivity reactions may occur in patients with or without a history of allergy or bronchial asthma.

The possibility of exacerbation or activation of systemic lupus erythematosus has been reported.

Lithium generally should not be given with diuretics (see PRECAUTIONS: Drug Interactions).

Acute Myopia and Secondary Angle-Closure Glaucoma:Hydrochlorothiazide, a sulfonamide, can cause an idiosyncratic reaction, resulting in acute transient myopia and acute angle-closure glaucoma. Symptoms include acute onset of decreased visual acuity or ocular pain and typically occur within hours to weeks of drug initiation. Untreated acute angle-closure glaucoma can lead to permanent vision loss. The primary treatment is to discontinue hydrochlorothiazide as rapidly as possible. Prompt medical or surgical treatments may need to be considered if the intraocular pressure remains uncontrolled. Risk factors for developing acute angle-closure glaucoma may include a history of sulfonamide or penicillin allergy.

PRECAUTIONS : General:

All patients receiving diuretic therapy should be observed for evidence of fluid or electrolyte imbalance: namely, hyponatremia, hypochloremic alkalosis, and hypokalemia. Serum and urine electrolyte determinations are particularly important when the patient is vomiting excessively or receiving parenteral fluids. Warning signs or symptoms of fluid and electrolyte imbalance, irrespective of cause, include dryness of mouth, thirst, weakness, lethargy, drowsiness, restlessness, confusion, seizures, muscle pains or cramps, muscular fatigue, hypotension, oliguria, tachycardia, and gastrointestinal disturbances such as nausea and vomiting.

Hypokalemia may develop, especially with brisk diuresis, when severe cirrhosis is present or after prolonged therapy.

Interference with adequate oral electrolyte intake will also contribute to hypokalemia. Hypokalemia may cause cardiac arrhythmia and may also sensitize or exaggerate the response of the heart to the toxic effects of digitalis (e.g., increased ventricular irritability). Hypokalemia may be avoided or treated by use of potassium sparing diuretics or potassium supplements such as foods with a high potassium content.

Although any chloride deficit is generally mild and usually does not require specific treatment except under extraordinary circumstances (as in liver disease or renal disease), chloride replacement may be required in the treatment of metabolic alkalosis.

Dilutional hyponatremia may occur in edematous patients in hot weather; appropriate therapy is water restriction, rather than administration of salt, except in rare instances when the hyponatremia is life threatening. In actual salt depletion, appropriate replacement is the therapy of choice. Hyperuricemia may occur or acute gout may be precipitated in certain patients receiving thiazides.

In diabetic patients dosage adjustments of insulin or oral hypoglycemic agents may be required. Hyperglycemia may occur with thiazide diuretics. Thus latent diabetes mellitus may become manifest during thiazide therapy.

The antihypertensive effects of the drug may be enhanced in the post-sympathectomy patient.

If progressive renal impairment becomes evident, consider withholding or discontinuing diuretic therapy.

Thiazides have been shown to increase the urinary excretion of magnesium; this may result in hypomagnesemia.

Thiazides may decrease urinary calcium excretion. Thiazides may cause intermittent and slight elevation of serum calcium in the absence of known disorders of calcium metabolism. Marked hypercalcemia may be evidence of hidden hyperparathyroidism. Thiazides should be discontinued before carrying out tests for parathyroid function.

Increases in cholesterol and triglyceride levels may be associated with thiazide diuretic therapy.

Laboratory Tests:

Periodic determination of serum electrolytes to detect possible electrolyte imbalance should be done at appropriate intervals.

Drug Interactions:

When given concurrently the following drugs may interact with thiazide diuretics.

Alcohol, Barbiturates, or Narcotics:Potentiation of orthostatic hypotension may occur.

Antidiabetic Drugs - (Oral Agents and Insulin):Dosage adjustment of the antidiabetic drug may be required.

Other Antihypertensive Drugs:Additive effect or potentiation.

Cholestyramine and Colestipol Resins:Absorption of hydrochlorothiazide is impaired in the presence of anionic exchange resins. Single doses of either cholestyramine or colestipol resins bind the hydrochlorothiazide and reduce its absorption from the gastrointestinal tract by up to 85% and 43%, respectively.

Corticosteroids, ACTH:Intensified electrolyte depletion, particularly hypokalemia.

Pressor amines (e.g., Norepinephrine):Possible decreased response to pressor amines but not sufficient to preclude their use.

Skeletal muscle relaxants, Nondepolarizing (e.g., Tubocurarine):Possible increased responsiveness to the muscle relaxant.

Lithium:Generally should not be given with diuretics. Diuretic agents reduce the renal clearance of lithium and add a high risk of lithium toxicity. Refer to the package insert for lithium preparations before use of such preparations with hydrochlorothiazide.

Non-Steroidal Anti-inflammatory Drugs:In some patients, the administration of a non-steroidal anti-inflammatory agent can reduce the diuretic, natriuretic, and antihypertensive effects of loop, potassium-sparing and thiazide diuretics. Therefore, when hydrochlorothiazide and non-steroidal anti-inflammatory agents are used concomitantly, the patient should be observed closely to determine if the desired effect of the diuretic is obtained.

Drug/Laboratory Test Interactions:

Thiazides should be discontinued before carrying out tests for parathyroid function (see PRECAUTIONS: General).

Carcinogenesis, Mutagenesis, Impairment of Fertility:Two-year feeding studies in mice and rats conducted under the auspices of the National Toxicology Program (NTP) uncovered no evidence of a carcinogenic potential of hydrochlorothiazide in female mice (at doses of up to approximately 600 mg/kg/day) or in male and female rats (at doses of up to approximately 100 mg/kg/day). The NTP, however, found equivocal evidence for hepatocarcinogenicity in male mice.

Hydrochlorothiazide was not genotoxic in vitroin the Ames mutagenicity assay of Salmonella typhimuriumstrains TA 98, TA 100, TA 1535, TA 1537, and TA 1538 and in the Chinese Hamster Ovary (CHO) test for chromosomal aberrations, or in vivoin assays using mouse germinal cell chromosomes, Chinese hamster bone marrow chromosomes, and the Drosophilasex-linked recessive lethal trait gene. Positive test results were obtained only in the in vitroCHO Sister Chromatid Exchange (clastogenicity) and in the Mouse Lymphoma Cell (mutagenicity) assays, using concentrations of hydrochlorothiazide from 43 to 1300 mcg/mL, and in the Aspergillus nidulansnon-disjunction assay at an unspecified concentration.

Hydrochlorothiazide had no adverse effects on the fertility of mice and rats of either sex in studies wherein these species were exposed, via their diet, to doses of up to 100 and 4 mg/kg, respectively, prior to conception and throughout gestation.

Pregnancy:

Teratogenic Effects - Pregnancy Category B:
Studies in which hydrochlorothiazide was orally administered to pregnant mice and rats during their respective periods of major organogenesis at doses up to 3000 and 1000 mg hydrochlorothiazide/kg, respectively, provided no evidence of harm to the fetus.

There are, however, no adequate and well-controlled studies in pregnant women. Because animal reproduction studies are not always predictive of human response, this drug should be used during pregnancy only if clearly needed.

NONTERATOGENIC EFFECTS

Nonteratogenic Effects:Thiazides cross the placental barrier and appear in cord blood. There is a risk of fetal or neonatal jaundice, thrombocytopenia, and possibly other adverse reactions that have occurred in adults.

Nursing Mothers:

Thiazides are excreted in breast milk. Because of the potential for serious adverse reactions in nursing infants, a decision should be made whether to discontinue nursing or to discontinue hydrochlorothiazide, taking into account the importance of the drug to the mother.

Pediatric Use:

There are no well-controlled clinical trials in pediatric patients. Information on dosing in this age group is supported by evidence from empiric use in pediatric patients and published literature regarding the treatment of hypertension in such patients (See DOSAGE AND ADMINISTRATION: Infants and Children).

Information for Patients

Non-melanoma Skin Cancer:Instruct patients taking hydrochlorothiazide to protect skin from the sun and undergo regular skin cancer screening.

ADVERSE REACTIONS:

The following adverse reactions have been reported and, within each category, are listed in order of decreasing severity.

Body as a Whole:Weakness

Cardiovascular:Hypotension including orthostatic hypotension (may be aggravated by alcohol, barbiturates, narcotics or antihypertensive drugs).

Digestive:Pancreatitis, jaundice (intrahepatic cholestatic jaundice), diarrhea, vomiting, sialadenitis, cramping, constipation, gastric irritation, nausea, anorexia.

Hematologic:Aplastic anemia, agranulocytosis, leukopenia, hemolytic anemia, thrombocytopenia.

Hypersensitivity:Anaphylactic reactions, necrotizing angiitis (vasculitis and cutaneous vasculitis), respiratory distress including pneumonitis and pulmonary edema, photosensitivity, fever, urticaria, rash, purpura.

Metabolic:Electrolyte imbalance (see PRECAUTIONS), hyperglycemia, glycosuria, hyperuricemia.

Musculoskeletal:Muscle spasm.

Nervous System/Psychiatric:Vertigo, paresthesias, dizziness, headache, restlessness.

Renal:Renal failure, renal dysfunction, interstitial nephritis (See WARNINGS).

Skin:Erythema multiforme including Stevens-Johnson Syndrome, exfoliative dermatitis including toxic epidermal necrolysis, alopecia.

Special Senses:Transient blurred vision, xanthopsia.

Urogenital:Impotence

Whenever adverse reactions are moderate or severe, thiazide dosage should be reduced or therapy withdrawn.

Postmarketing Experience

Non-melanoma Skin Cancer
Hydrochlorothiazide is associated with an increased risk of non-melanoma skin cancer. In a study conducted in the Sentinel System, increased risk was predominantly for squamous cell carcinoma (SCC) and in white patients taking large cumulative doses. The increased risk for SCC in the overall population was approximately 1 additional case per 16,000 patients per year, and for white patients taking a cumulative dose of ≥50,000 mg the risk increase was approximately 1 additional SCC case for every 6,700 patients per year.

OVERDOSAGE:

The most common signs and symptoms observed are those caused by electrolyte depletion (hypokalemia, hypochloremia, hyponatremia) and dehydration resulting from excessive diuresis. If digitalis has also been administered, hypokalemia may accentuate cardiac arrhythmias.

In the event of overdosage, symptomatic and supportive measures should be employed. Emesis should be induced or gastric lavage performed. Correct dehydration, electrolyte imbalance, hepatic coma and hypotension by established procedures. If required, give oxygen or artificial respiration for respiratory impairment. The degree to which hydrochlorothiazide is removed by hemodialysis has not been established.

The oral LD50of hydrochlorothiazide is greater than 10 g/kg in the mouse and rat.

DOSAGE AND ADMINISTRATION:

Therapy should be individualized according to patient response. Use the smallest dosage necessary to achieve the required response.

Adults: For Edema:The usual adult dosage is 25 to 100 mg daily as a single or divided dose. Many patients with edema respond to intermittent therapy, i.e., administration on alternate days or on 3 to 5 days each week. With an intermittent schedule, excessive response and the resulting undesirable electrolyte imbalance are less likely to occur.

For Control of Hypertension:The usual initial dose in adults is 25 mg daily given as a single dose. The dose may be increased to 50 mg daily, given as a single or two divided doses. Doses above 50 mg are often associated with marked reductions in serum potassium (see also PRECAUTIONS).

Patients usually do not require doses in excess of 50 mg of hydrochlorothiazide daily when used concomitantly with other antihypertensive agents.

Infants and Children: For Diuresis and for Control of Hypertension:The usual pediatric dosage is 0.5 mg to 1 mg per pound (1 to 2 mg/kg) per day in single or two divided doses, not to exceed 37.5 mg per day in infants up to 2 years of age or 100 mg per day in children 2 to 12 years of age. In infants less than 6 months of age, doses up to 1.5 mg per pound (3 mg/kg) per day in two divided doses may be required (See PRECAUTIONS: Pediatric Use).

HOW SUPPLIED:

Hydrochlorothiazide tablets, USP are available containing 12.5 mg, 25 mg and 50 mg hydrochlorothiazide, USP.

The 12.5 mg tablets are light orange to peach colored, round, biconvex tablets debossed with H on one side and 1 on another side. They are available as follows:

Bottle of 100 tablets with a child-resistant closure NDC 16729-182-01

Bottle of 1,000 tablets NDC 16729-182-17

The 25 mg tablets are light orange to peach colored, round, flat tablets with beveled edges and debossed with H & 2 on either side of break line and another side is plain. They are available as follows:

Bottle of 100 tablets with a child-resistant closure NDC 16729-183-01
Bottle of 1,000 tablets NDC 16729-183-17

The 50 mg tablets are light orange to peach colored, round, flat tablets with beveled edges and debossed with H & 3 on either side of break line and another side is plain. They are available as follows:

Bottle of 100 tablets with a child-resistant closure NDC 16729-184-01
Bottle of 1,000 tablets NDC 16729-184-17

STORAGE AND HANDLING

Store at 20° to 25°C (68° to 77°F). [See USP for Controlled Room Temperature].

Dispense in a tight, light-resistant container as defined in the USP, using a child-resistant closure.

For more information, go to www.accordhealthcare.usor call Accord Healthcare at 1-866-941-7875.

Manufactured For:
Accord Healthcare, Inc.,
8041 Arco Corporate Drive,
Suite 200,
Raleigh, NC 27617,
USA.

Manufactured By:
Intas Pharmaceuticals Limited,
Ahmedabad -380 054, India

10 4475 1 6034504

Issued March 2025

12.5 mg Container Label

NDC 16729- 182-01

100Tablets

accord

25 mg Container Label

NDC 16729- 183-01

100Tablets

accord

50 mg Container Label

NDC 16729- 184-01

100Tablets

accord